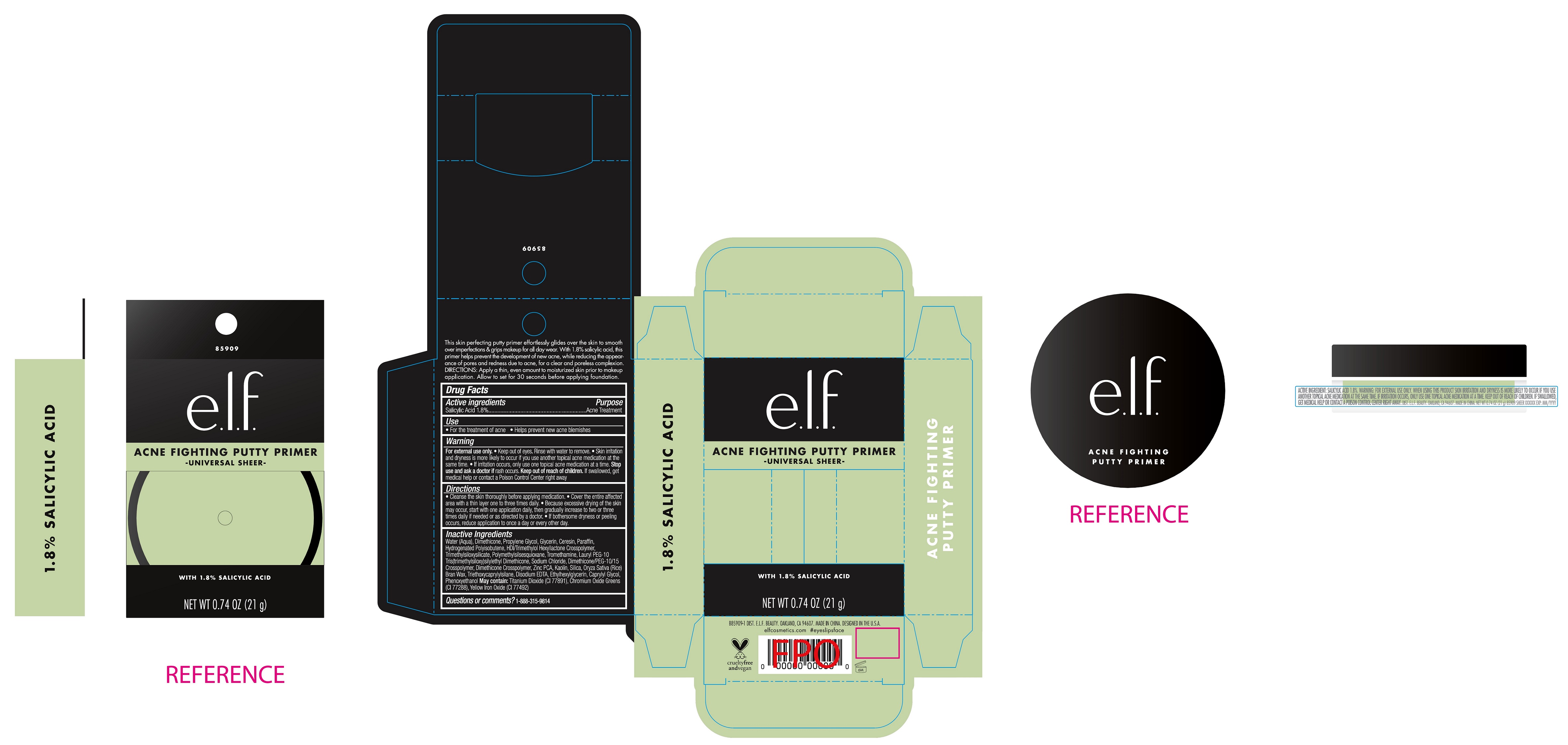 DRUG LABEL: Acne Fighting Putty Primer
NDC: 76354-412 | Form: CREAM
Manufacturer: e.l.f. Cosmetics, Inc
Category: otc | Type: HUMAN OTC DRUG LABEL
Date: 20251021

ACTIVE INGREDIENTS: SALICYLIC ACID 18 mg/1 g
INACTIVE INGREDIENTS: ZINC PIDOLATE; KAOLIN; SILICON DIOXIDE; RICE BRAN; TRIETHOXYCAPRYLYLSILANE; EDETATE DISODIUM ANHYDROUS; ETHYLHEXYLGLYCERIN; CAPRYLYL GLYCOL; PHENOXYETHANOL; WATER; DIMETHICONE; PROPYLENE GLYCOL; GLYCERIN; CERESIN; PARAFFIN; HYDROGENATED POLYBUTENE (1300 MW); HEXAMETHYLENE DIISOCYANATE/TRIMETHYLOL HEXYLLACTONE CROSSPOLYMER; POLYMETHYLSILSESQUIOXANE (4.5 MICRONS); TROMETHAMINE; DIMETHICONE/PEG-10/15 CROSSPOLYMER

Acne Fighting Putty Primer

Active ingredients

Salicylic Acid 1.8%

Purpose

Acne Treatment

Use

- For the treatment of acne
- Helps prevent new acne blemishes

Warnings

For external use only.

- Keep out of eyes. Rinse with water to remove.
- Skin irritation and dryness is more likely to occur if you use another topical acne medication at a time.

Stop use and ask a doctor if

rash occurs.

Keep out of reach of children.

If swallowed, get medical help or contact a Poison Control Center right away

Directions

- Cleanse the skin thoroughly before applying medication.
- Cover the entire affected area with a thin layer one to three times daily.
- Because excessive drying of the skin may occur, start with one application daily, then gradually increase to two or three times daily if needed or as directed by a doctor.
- If bothersome dryness or peeling occurs, reduce application to once a day every other day.

Inactive Ingredients

Water (Aqua), Dimethicone, Propylene Glycol, Glycerin, Ceresin, Paraffin, Hydrogenated Polyisobutene, HDI/Trimethylol Hexyllactone Crosspolymer, Trimethylsiloxysilicate, Polymethylsilsesquioxane, Tromethamine, Tromethamine Sodium Chloride, Dimethicone/PEG-10/15 Crosspolymer, Dimethicone Crosspolymer, Zinc PCA, Kaolin, Silica, Oryza Sativa (Rice) Bran Wax, Triethoxycaprylylsilane, Disodium EDTA, Ethylhexylglycerin, Caprylyl Glycol, Phenoxyethanol May contain: Titanium Dioxide (CI 77891), Chromium Oxide Greens (CI 77288), Yellow Iron Oxide (CI 77492)

Questions or comments?

1-888-315-9814